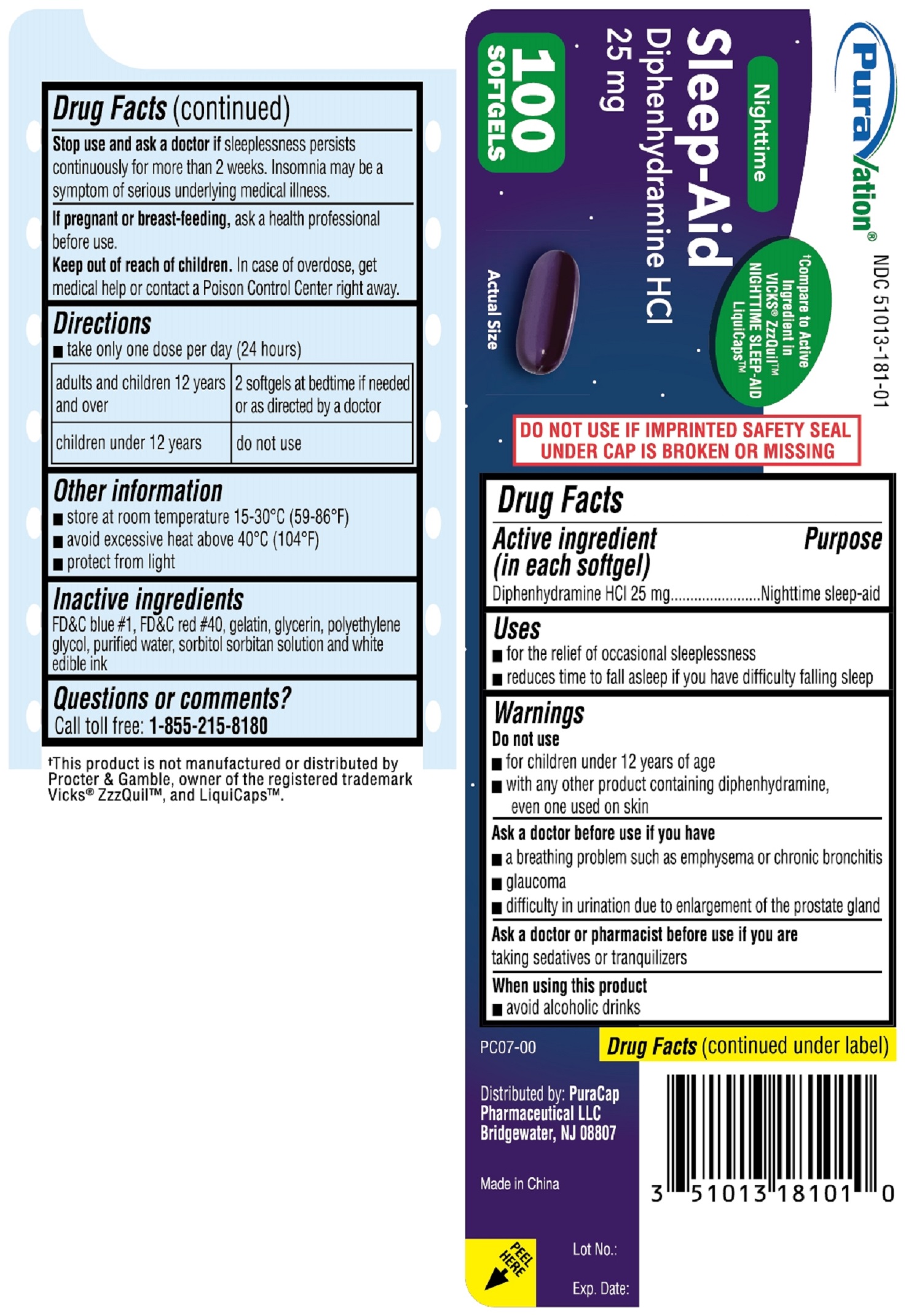 DRUG LABEL: Nighttime SLEEP AID
NDC: 51013-181 | Form: CAPSULE, LIQUID FILLED
Manufacturer: PuraCap Pharmaceutical LLC
Category: otc | Type: HUMAN OTC DRUG LABEL
Date: 20241119

ACTIVE INGREDIENTS: DIPHENHYDRAMINE HYDROCHLORIDE 25 mg/1 1
INACTIVE INGREDIENTS: FD&C BLUE NO. 1; FD&C RED NO. 40; GELATIN; GLYCERIN; POLYETHYLENE GLYCOL, UNSPECIFIED; WATER; SORBITOL

Diphenhydramine Hydrochloride

Drug Facts

Active ingredient (in each softgel)

Diphenhydramine HCl 25 mg

Purpose

Nighttime sleep-aid

Uses

- for the relief of occasional sleeplessness
- reduces time to fall asleep if you have difficulty falling asleep

Warnings

Do not use

- for children under 12 years of age
- with any other product containing diphenhydramine, even one used on skin

Ask a doctor before use if you have

- a breathing problem such as emphysema or chronic bronchitis
- glaucoma
- difficulty in urination due to enlargement of the prostate gland

Ask a doctor or pharmacist before use if you are taking sedatives or tranquilizers

When using this product

- avoid alcoholic drinks

Stop use and ask a doctor if sleeplessness persists continuously for more than 2 weeks. Insomnia may be a symptom of serious underlying medical illness.

PREGNANCY OR BREAST FEEDING

If pregnant or breast-feeding, ask a health professional before use.

Keep out of reach of children.

OVERDOSAGE

In case of overdose, get medical help or contact a Poison Control Center right away.

Directions

- take only one dose per day (24 hours)

adults and children 12 years and over | 2 softgels at bedtime if needed or as directed by a doctor
children under12 years | do not use

Other information

- store at room temperature 15°-30° C (59°-86° F)
- avoid excessive heat above 40° C (104° F)
- protect from light

Inactive ingredients

FD&C blue #1, FD&C red #40, gelatin, glycerin, polyethylene glycol, purified water, sorbitol sorbitan solution and white edible ink

Questions or comments?

Call toll free: 1-855-215-8180

PRINCIPAL DISPLAY PANEL

Nighttime SLEEP-AID

Diphenhydramine HCl 25mg

100 SOFTGELS

Compare to Active Ingredient in VICKS® ZzzQuilTM NIGHTTIME SLEEP-AID LiquiCapsTM

NDC 51013-181-01